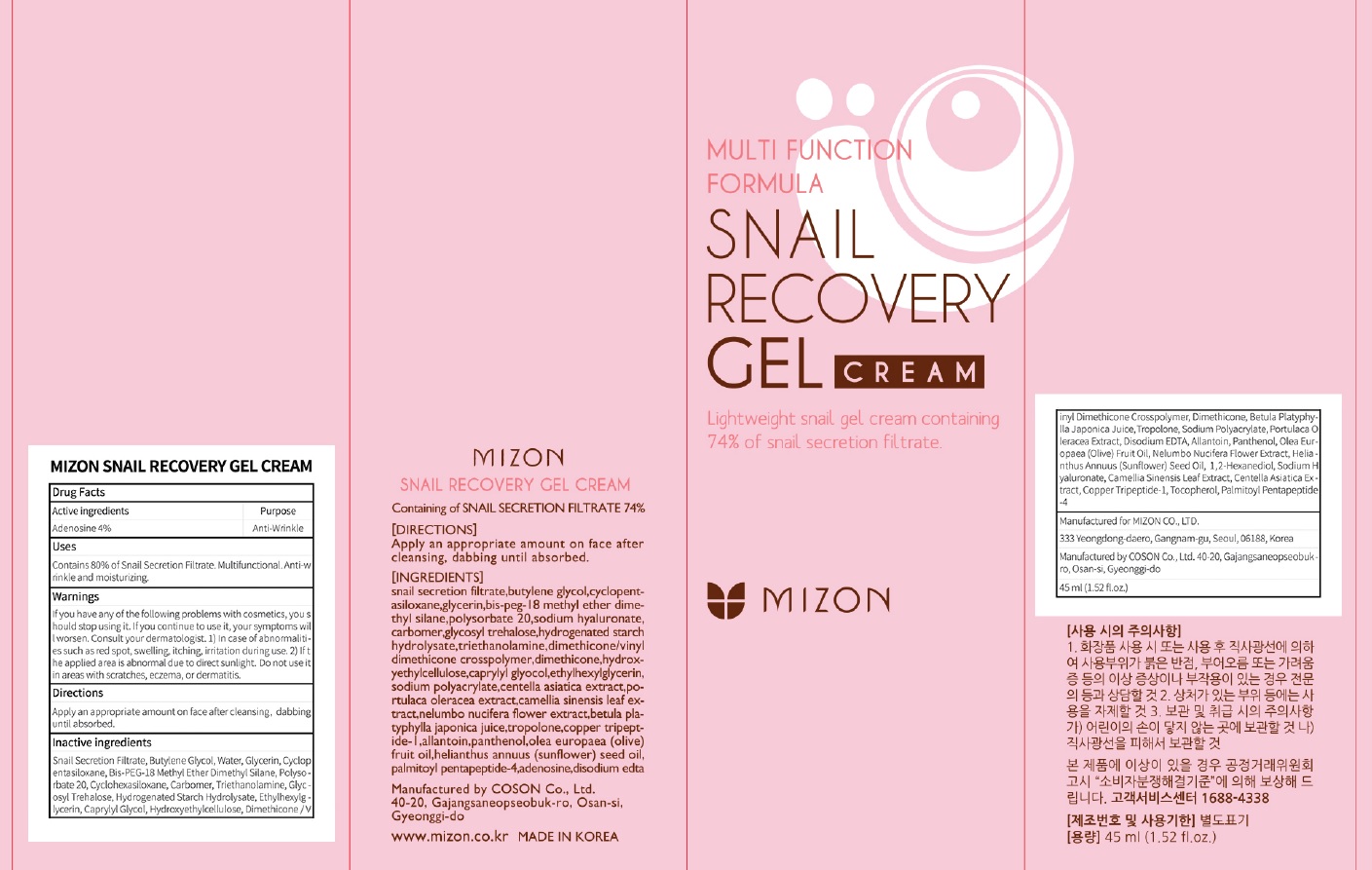 DRUG LABEL: MIZON SNAIL RECOVERY GE L CREA M
NDC: 57718-270 | Form: CREAM
Manufacturer: MIZON CO.,LTD.
Category: otc | Type: HUMAN OTC DRUG LABEL
Date: 20180724

ACTIVE INGREDIENTS: Adenosine 0.018 g/45 mL
INACTIVE INGREDIENTS: Butylene Glycol; Water

ACTIVE INGREDIENT

Active ingredients: Adenosine 0.04%

INACTIVE INGREDIENT

Inactive ingredients:

Snail Secretion Filtrate, Butylene Glycol, Water, Glycerin, Cyclopentasiloxane, Bis-PEG-18 Methyl Ether Dimethyl Silane, Polysorbate 20, Cyclohexasiloxane, Carbomer, Triethanolamine, Glycosyl Trehalose, Hydrogenated Starch Hydrolysate, Ethylhexylglycerin, Caprylyl Glycol, Hydroxyethylcellulose, Dimethicone/Vinyl Dimethicone Crosspolymer, Dimethicone, Betula Platyphylla Japonica Juice, Tropolone, Sodium Polyacrylate, Portulaca Oleracea Extract, Disodium EDTA, Allantoin, Panthenol, Olea Europaea (Olive) Fruit Oil, Nelumbo Nucifera Flower Extract, Helianthus Annuus (Sunflower) Seed Oil, 1,2-Hexanediol, Sodium Hyaluronate, Camellia Sinensis Leaf Extract, Centella Asiatica Extract, Copper Tripeptide-1, Tocopherol, Palmitoyl Pentapeptide-4

PURPOSE

Purpose: Anti Wrinkle

WARNINGS

If you have any of the following problems with cosmetics, you should stop using it. If you continue to use it, your symptoms will worsen. Consult your dermatologist. 1) In case of abnormalities such as red spot, swelling, itching, irritation during use. 2) If the applied area is abnormal due to direct sunlight. Do not use it in areas with scratches, eczema, or dermatitis.

KEEP OUT OF REACH OF CHILDREN

Uses

Contains 80% of Snail Secretion Filtrate. Multifunctional. Anti-wrinkle and moisturizing.

Directions

Apply an appropriate amount on face after cleansing, dabbing until absorbed.